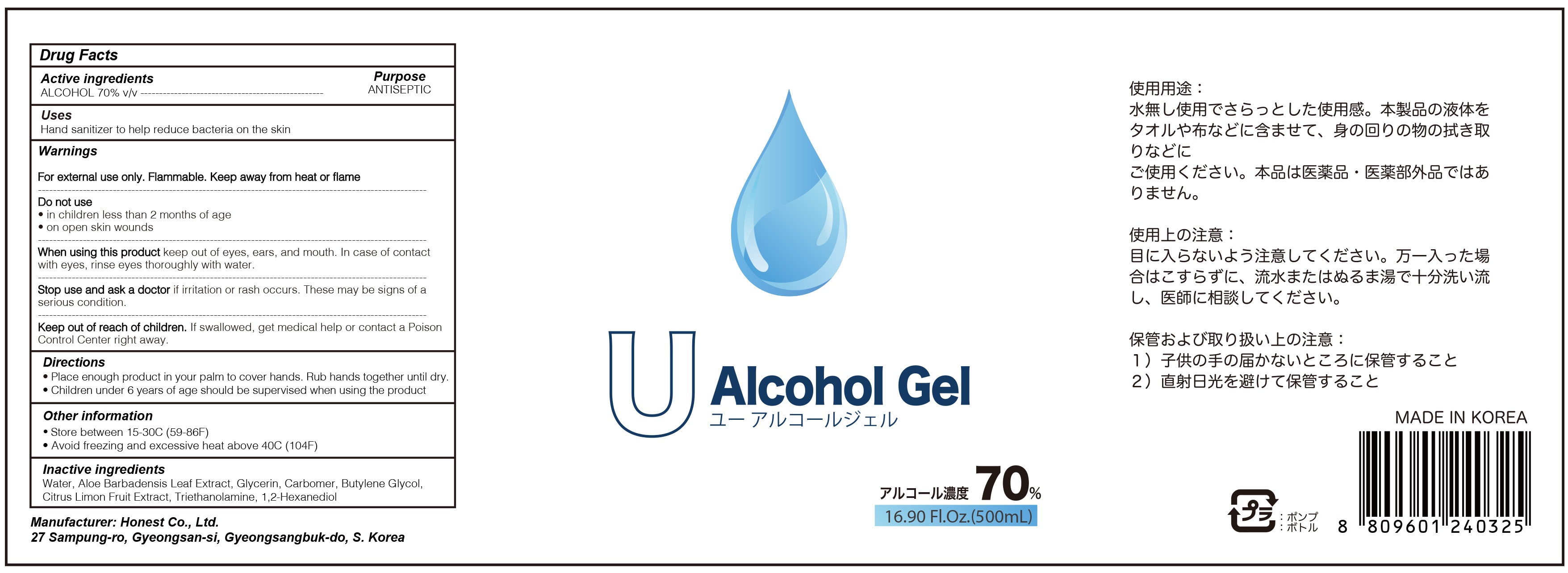 DRUG LABEL: U Alcohol
NDC: 76904-100 | Form: GEL
Manufacturer: Honest Co., Ltd.
Category: otc | Type: HUMAN OTC DRUG LABEL
Date: 20200527

ACTIVE INGREDIENTS: ALCOHOL 350 mL/500 mL
INACTIVE INGREDIENTS: Water; ALOE VERA LEAF; Glycerin; CARBOMER HOMOPOLYMER, UNSPECIFIED TYPE; Butylene Glycol; LEMON; TROLAMINE; 1,2-Hexanediol

ACTIVE INGREDIENT

ALCOHOL 70% v/v

INACTIVE INGREDIENTS

Water, Aloe Barbadensis Leaf Extract, Glycerin, Carbomer, Butylene Glycol, Citrus Limon Fruit Extract, Triethanolamine, 1,2-Hexanediol

PURPOSE

ANTISEPTIC

WARNINGS

For external use only. Flammable. Keep away from heat or flame

--------------------------------------------------------------------------------------------------------
Do not use
• in children less than 2 months of age
• on open skin wounds
--------------------------------------------------------------------------------------------------------
When using this product keep out of eyes, ears, and mouth. In case of contact with eyes, rinse eyes thoroughly with water.
--------------------------------------------------------------------------------------------------------
Stop use and ask a doctor if irritation or rash occurs. These may be signs of a serious condition.

KEEP OUT OF REACH OF CHILDREN

If swallowed, get medical help or contact a Poison Control Center right away.

Uses

Hand sanitizer to help reduce bacteria on the skin

Directions

• Place enough product in your palm to cover hands. Rub hands together until dry.

• Children under 6 years of age should be supervised when using the product

Other information

• Store between 15-30C (59-86F)
• Avoid freezing and excessive heat above 40C (104F)